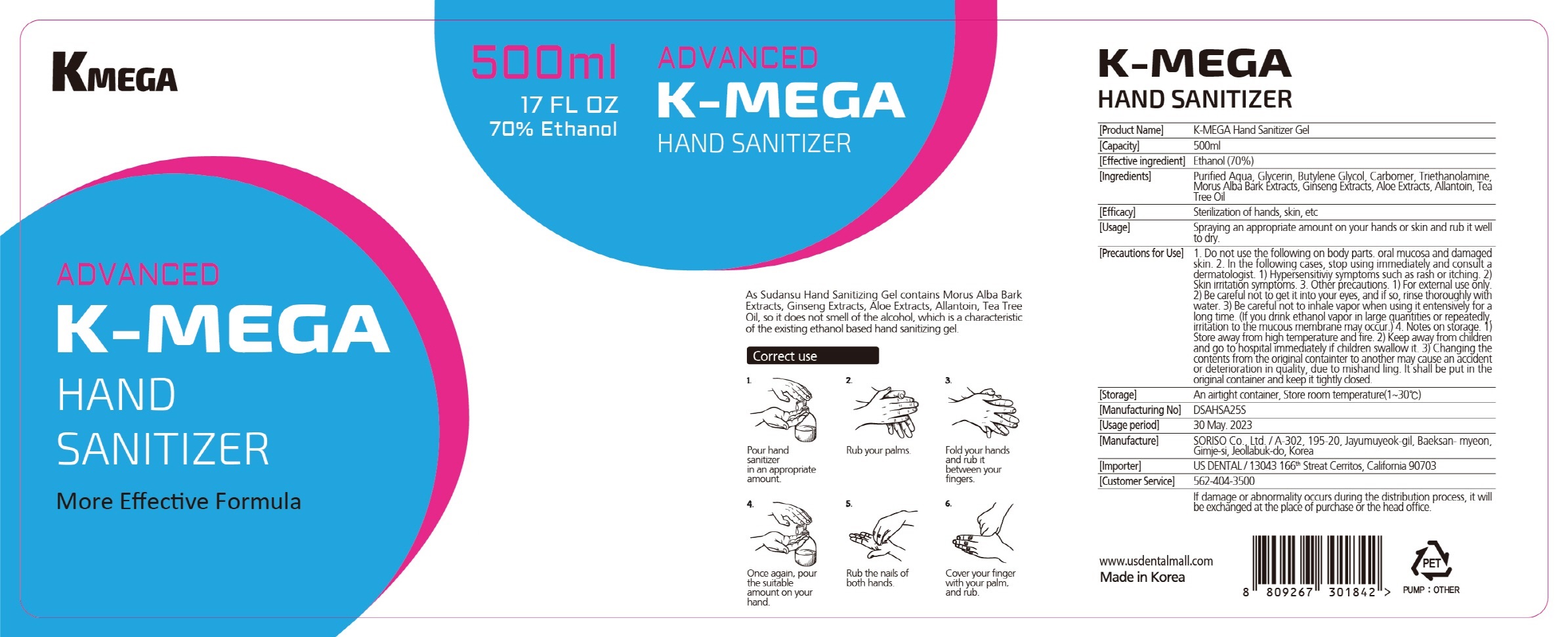 DRUG LABEL: K-MEGA Hand Sanitizer
NDC: 69969-700 | Form: GEL
Manufacturer: Soriso
Category: otc | Type: HUMAN OTC DRUG LABEL
Date: 20200617

ACTIVE INGREDIENTS: ALCOHOL 350 mL/500 mL
INACTIVE INGREDIENTS: GLYCERIN; WATER; CARBOMER HOMOPOLYMER, UNSPECIFIED TYPE; TROLAMINE

Drug Facts

ACTIVE INGREDIENT

Alcohol

INACTIVE INGREDIENT

Water
Glycerin
Butylene Glycol
Carbomer
Triethanolamine
Mulberry Root Extract
Aloe Extract
Allantoin
Tea Tree Oil

PURPOSE

Antiseptic

KEEP OUT OF REACH OF THE CHILDREN

INDICATIONS AND USAGE

For the external use only

WARNINGS

For external use only.

Flammable, keep away from fire or flame.

When using this product keep out of eyes. If contact with eyes occurs, rinse promptly and thoroughly with water.

Stop use and ask a doctor if significant irritation or sensitization develops.

Keep out of reach of children. If swallowed, get medical help or contact a Poison Control Center right away.

DOSAGE AND ADMINISTRATION

Spraying an appropriate amount on your hands or skin and rub it well to dry.